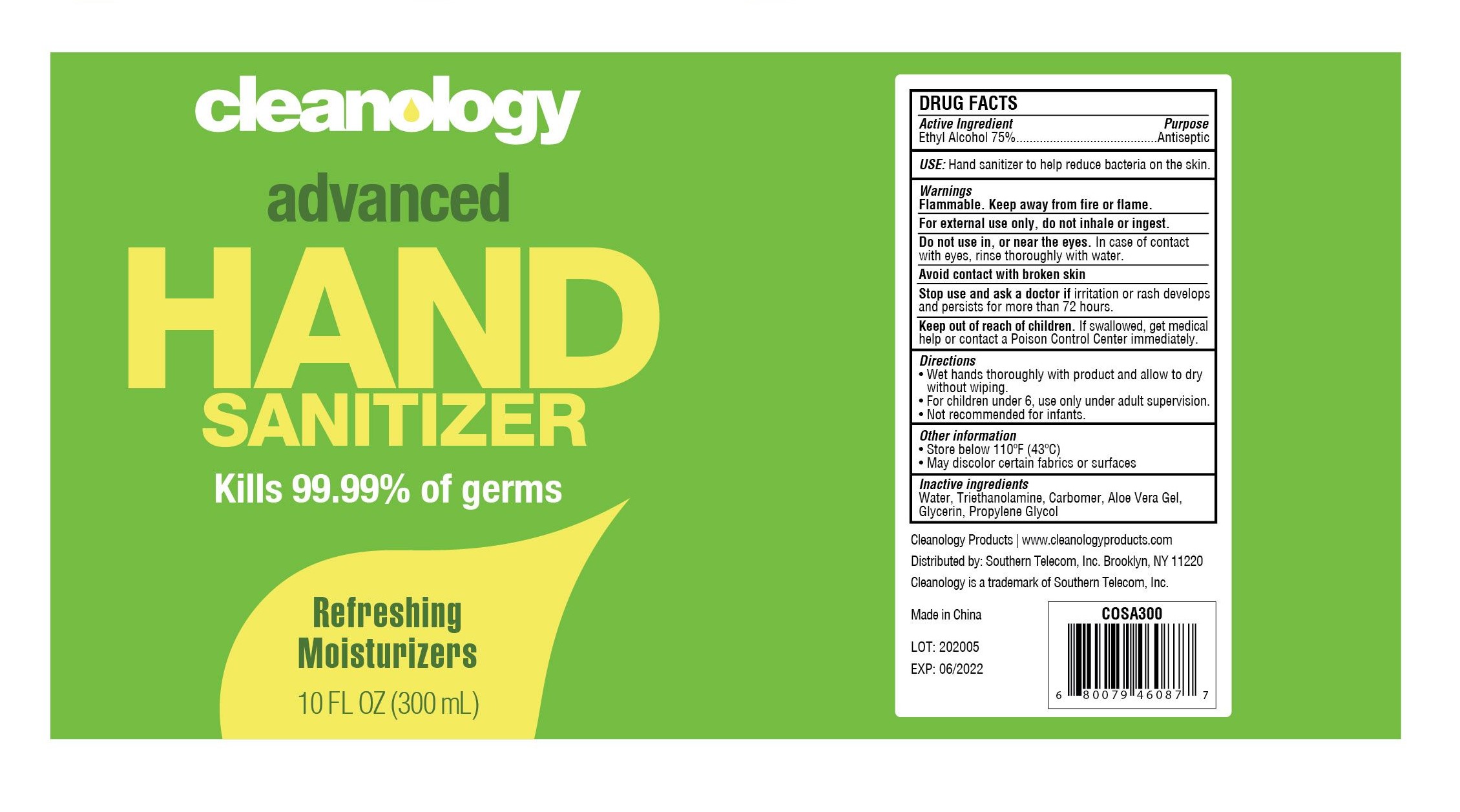 DRUG LABEL: Hand Sanitizer
NDC: 76546-001 | Form: LIQUID
Manufacturer: Southern Telecom, Inc.
Category: otc | Type: HUMAN OTC DRUG LABEL
Date: 20200610

ACTIVE INGREDIENTS: ALCOHOL 75 mL/100 mL
INACTIVE INGREDIENTS: PROPYLENE GLYCOL; ALOE VERA LEAF; CARBOMER HOMOPOLYMER, UNSPECIFIED TYPE; WATER; TROLAMINE; GLYCERIN

Cleanology, Colorways, Advanced Hand Sanitizer

Active Ingredient

Alcohol 75%

Purpose

Antiseptic

Use

Hand sanitizer to help reduce bacteria on the skin.

Warnings

Flammable. Keep away from fire or flame.

For external use only, do not inhale or ingest.

Do not use

in, or near the eyes. In case of contact with eyes, rinse thoroughly with water.

Avoid contact with broken skin

Stop use and ask a doctor if

redness or irritation develops, irritation or rash develop and persist for more than 72 hours.

Keep out of reach of children

if swallowed, get medical help or contact a Poison Control Center immediately.

Directions

- Wet hands thoroughly with product and allow to dry without wiping.
- For children under 6, use only under adult supervision.
- Not recommended for infants.

Other information

- Store below 110°F (43°C)
- May discolor certain fabrics or surfaces

Inactive ingredients

Water, Triethanolamine, Carbomer, Aloe Vera Gel, Fragrance, Glycerin, Propylene Glycol